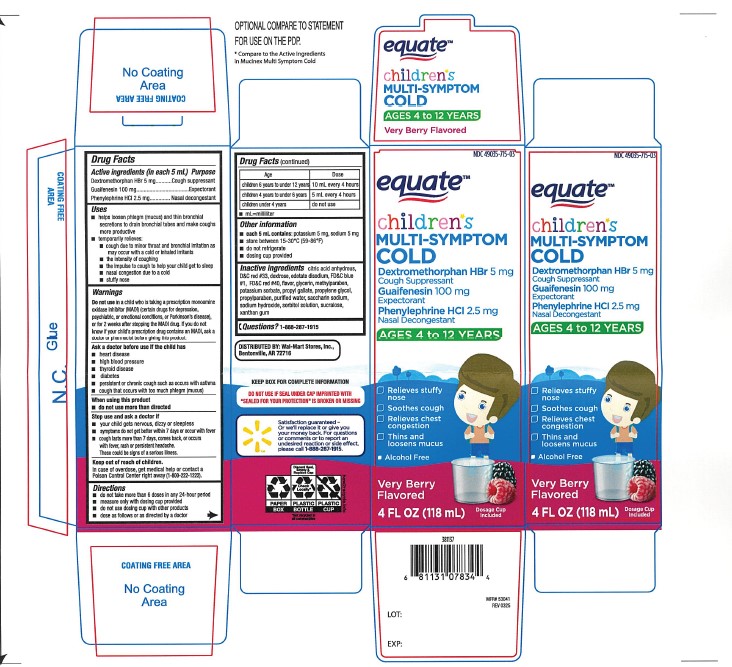 DRUG LABEL: Childrens Multi-symptom Cold
NDC: 49035-715 | Form: LIQUID
Manufacturer: Wal-Mart Stores, Inc.
Category: otc | Type: Human OTC Drug Label
Date: 20251203

ACTIVE INGREDIENTS: DEXTROMETHORPHAN HYDROBROMIDE 5 mg/5 mL; GUAIFENESIN 100 mg/5 mL; PHENYLEPHRINE HYDROCHLORIDE 2.5 mg/5 mL
INACTIVE INGREDIENTS: ANHYDROUS CITRIC ACID; D&C RED NO. 33; DEXTROSE; EDETATE DISODIUM; FD&C BLUE NO. 1; FD&C RED NO. 40; GLYCERIN; METHYLPARABEN; POTASSIUM SORBATE; PROPYL GALLATE; PROPYLENE GLYCOL; PROPYLPARABEN; WATER; SACCHARIN SODIUM; SODIUM HYDROXIDE; SORBITOL; SUCRALOSE; XANTHAN GUM

Equate Children's Multi-Symptom Cold

ACTIVE INGREDIENT(S)

Dextromethorphan HBr 5mg

Guaifenesin 100 mg

Phenyephrine HCl 2.5 mg

PURPOSE

Cough Suppressant

Expectorant

Phenylephrine HCl

USE(S)

- helps loosen phlegm (mucus) and thin bronchial secretions to drain bronchial tubes and make coughs more productive
- temporarily relieves:
- cough due to minor throat and bronchial irritation as may occur with the common cold or inhaled irritants
- the intensity of coughing
- the impulse to cough to help your child get to sleep
- nasal congestion due to a cold
- stuffy nose

WARNINGS

.

DO NOT USE

in a child who is taking a prescription monoamine oxidase inhibitor (MAOI) (certain drugs for depression, psychiatric, or emotional conditions, or Parkinson's disease), or for 2 weeks after stopping the MAOI drug. If you do not know if your child's prescription drug contains an MAOI, ask a doctor or pharmacist before giving this product.

ASK A DOCTOR BEFORE USE IF

- heart disease
- high blood pressure
- thyroid disease
- diabetes
- persistent or chronic cough such as occurs with asthma
- cough that occurs with too much phlegm (mucus)

WHEN USING THIS PRODUCT

do not use more than directed

STOP USE AND ASK DOCTOR IF

- your child gets nervous, dizzy or sleepless
- symptoms do not get better within 7 days or occur with fever
- cough lasts more than 7 days, comes back, or occurs with fever, rash, or persistent headache.

These could be signs of a serious illness.

KEEP OUT OF REACH OF CHILDREN

In case of overdose, get medical help or contact a Poison Control Center right away.

DIRECTIONS

- do not take more than 6 doses in any 24-hour period
- measure only with dosing cup provided
- do not use dosing cup with other products
- dose as follows or as directed by a doctor
- mL = milliliter

Age | Dose
children 6 years to under 12 years | 10 mL every 4 hours
children 4 years to under 6 years | 5 mL every 4 hours
children under 4 years | do not use

OTHER INFORMATION

- each 5 mL contains: potassium 5 mg, sodium 5 mg
- store between 15-30°C (59-86°F)
- do not refrigerate
- dosing cup provided

INACTIVE INGREDIENTS

anhydrous citric acid, D&C red # 33, dextrose, edetate disodium, FD&C blue # 1, FD&C Red #40, flavor, glycerin, methylparaben, potassium sorbate, propylene glycol, propyl gallate, purified water, saccharin sodium, sodium hydroxide, sorbitol solution, sucralose, xanthan gum

PRINCIPAL DISPLAY PANEL

NDC 49035-715-03

equateTM

Compare to Children's Mucinex® Multi-Symptom Cold active ingredients*

Children's

Multi-Symptom Cold

Dextromethorphan HBr 5 mg

Cough Suppressant

Guaifenesin 100 mg

Expectorant

Phenylephrine HCl 2.5 mg

Nasal Decongestant

Ages 4 to 12 years

- Relieves Stuffy Nose
- Soothes Cough
- Relieves Chest Congestion
- Thins and loosens Mucus
- Alcohol Free

Very Berry Flavored
4 FL OZ (118 mL)